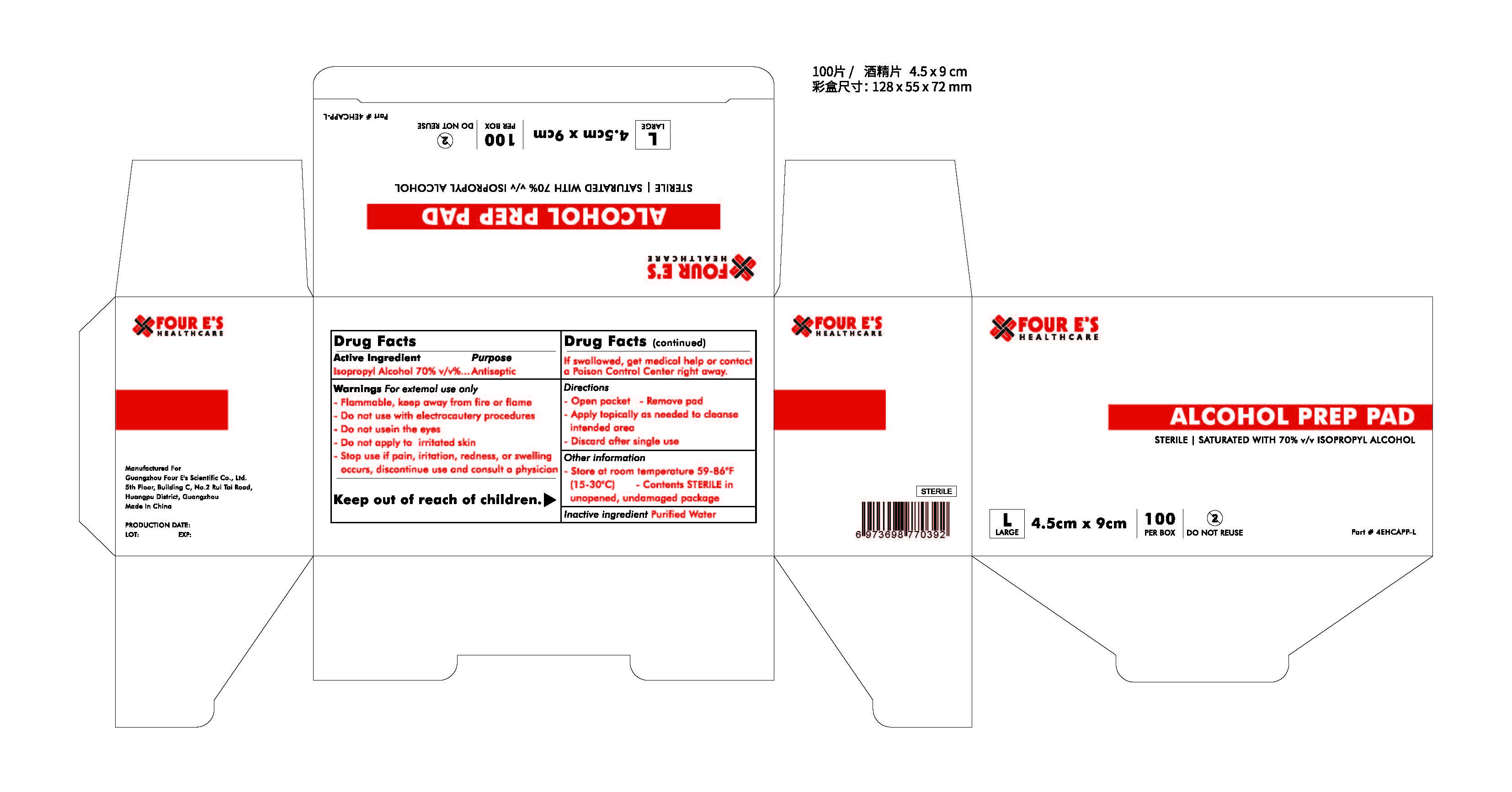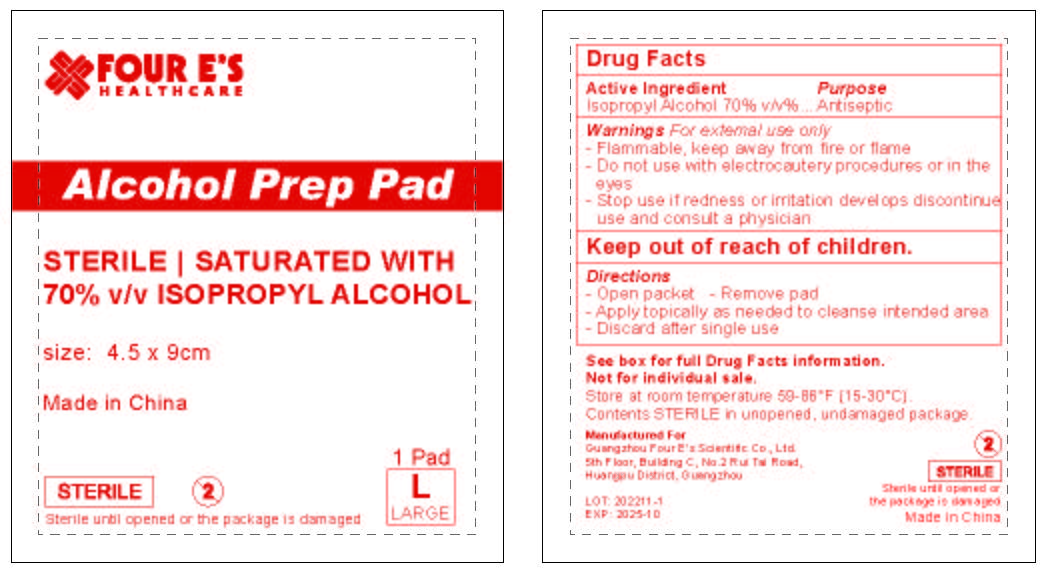 DRUG LABEL: Non-proprietary name
NDC: 83118-015 | Form: SWAB
Manufacturer: Guangzhou Four E's Scientific Co., Ltd.
Category: otc | Type: HUMAN OTC DRUG LABEL
Date: 20250818

ACTIVE INGREDIENTS: ISOPROPYL ALCOHOL 1.59 g/1 1
INACTIVE INGREDIENTS: WATER

Alcohol Prep Pad

Active Ingredient

Isopropyl Alcohol, 70% v/v

Purpose

Antiseptic

Warnings

For external use only

- Flammable, keep away from fire or flame

- Do not use with electrocautery procedures

- Do not use in the eyes

- Do not apply to irritated skin

- Stop use if pain, irritation, redness, or swelling occurs, discontinue use and consult a physician

Keep out of reach of children

Directions

- Open Packet -Remove Pad

- Apply topically as needed to cleanse intended area

- Discard after single use

Inactive Ingrdient

Purified Water

Other Information

- Store at room temperature 59-86°F (15-30°C)

- Content STERILE in unopened, undamaged package

Keep out of reach of children

Purpose

Antiseptic